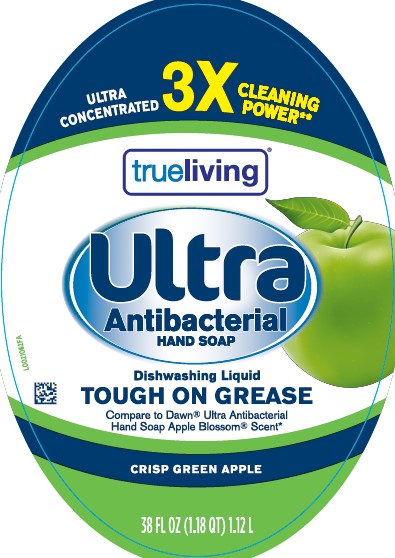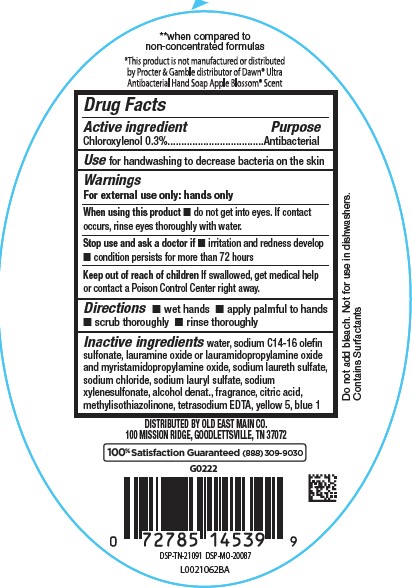 DRUG LABEL: Ultra
NDC: 55910-589 | Form: LIQUID
Manufacturer: Old East Main Co.
Category: otc | Type: HUMAN OTC DRUG LABEL
Date: 20260302

ACTIVE INGREDIENTS: CHLOROXYLENOL 3 mg/1 mL
INACTIVE INGREDIENTS: WATER; SODIUM C14-16 OLEFIN SULFONATE; LAURAMINE OXIDE; LAURAMIDOPROPYLAMINE OXIDE; MYRISTAMIDOPROPYLAMINE OXIDE; SODIUM LAURETH SULFATE; SODIUM CHLORIDE; SODIUM LAURYL SULFATE; SODIUM XYLENESULFONATE; ALCOHOL; CITRIC ACID MONOHYDRATE; METHYLISOTHIAZOLINONE; EDETATE SODIUM; FD&C YELLOW NO. 5; FD&C BLUE NO. 1

True Living 956.004/956AF
Crisp Green Apple Antibacterial Hand Soap

Disclaimer

Do not add bleach.

Not for use in dishwashers.

Contains Surfactants

*This product is not manufactured or distributed by Proctor & Gamble, distributor of Dawn® Ultra Antibacterial Hand Soap Apple Blossom® Scent.

**when compared to non-concentrated formulas

Active ingredient

Chloroxylenol 0.3%

Purpose

Antibacterial

Use

for handwashing to decrease bacteria on the skin

Warnings

For external use only: hands only

When using this product

- do not get into eyes. If contact occurs, rinse eyes thoroughly with water.

Stop use and ask a doctor if

- irritation and redness develop
- condition persists for more than 72 hours

Keep out of reach of children.

If swallowed, get medical help or contact a Poison Control Center right away.

Directions

- wet hands
- apply palmful to hands
- scrub thoroughly
- rinse thoroughly

Inactive ingredients

water, sodium C14-16 olefin sulfonate, lauramine oxide or lauramidopropylamine oxide and myristamidopropylamine oxide, sodium laureth sulfate, sodium chloride, sodium lauryl sulfate, sodium xylenesulfonate, alcohol denat., fragrance, citric acid, methylisothiazolinone, tetrasodium EDTA, yellow 5, blue 1

Adverse reaction

DISTRIBUTED BY OLD EAT MAIN CO.

100 MISSION RIDGE, GOODLETTSVILLE, TN 37072

100% Satisfaction Guarnateed! (888)309-9030

DSP-TN-21091 DSP-MO-20087

Principal display panel

ULTRA CONCENTRATED 3X CLEANING POWER**

trueliving®

Ultra Antibacterial Hand Soap

Dishwashing Liquid

TOUGH ON GREASE

Compare to Dawn®Ultra Antibacterial Hand Soap Apple Blossom®Scent*

CRISP GREEN APPLE

38 FL OZ (1.18 QT) 1.12 L